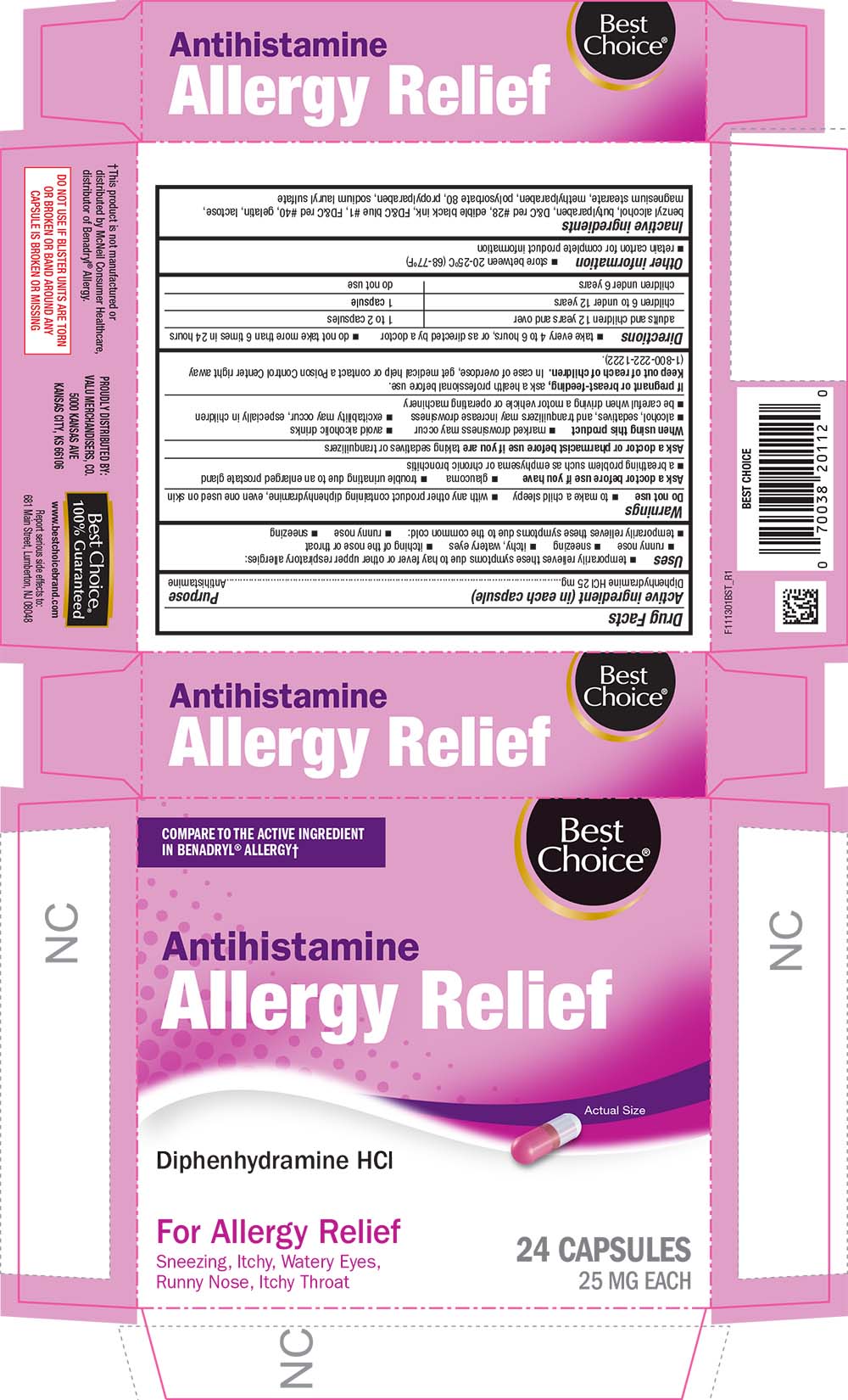 DRUG LABEL: Allergy Relief
NDC: 63941-413 | Form: CAPSULE
Manufacturer: VALU MERCHANDISERS COMPANY
Category: otc | Type: HUMAN OTC DRUG LABEL
Date: 20251211

ACTIVE INGREDIENTS: DIPHENHYDRAMINE HYDROCHLORIDE 25 mg/1 1
INACTIVE INGREDIENTS: BENZYL ALCOHOL; BUTYLPARABEN; D&C RED NO. 28; FD&C BLUE NO. 1; FD&C RED NO. 40; GELATIN; LACTOSE; MAGNESIUM STEARATE; METHYLPARABEN; POLYSORBATE 80; PROPYLPARABEN; SODIUM LAURYL SULFATE

1113-BST-2021-1117

Drug Facts

Active ingredient (in each capsule)

Diphenhydramine HCl 25 mg

Purpose

Antihistamine

Uses

- temporarily relieves these symptoms due to hay fever or other upper respiratory allergies:
  - runny nose
  - sneezing
  - itchy, watery eyes
  - itching of the nose or throat
- temporarily relieves these symptoms due to the common cold:
  - runny nose
  - sneezing

Warnings

Do not use with any other product containing diphenhydramine, even one used on skin

Ask a doctor before use if you have

- glaucoma
- trouble urinating due to an enlarged prostate gland
- a breathing problem such as emphysema or chronic bronchitis

Ask a doctor or pharmacist before use if you are taking sedatives or tranquilizers

When using this product

- marked drowsiness may occur
- avoid alcoholic drinks
- alcohol, sedatives, and tranquilizers may increase drowsiness
- excitability may occur, especially in children
- be careful when driving a motor vehicle or operating machinery

PREGNANCY OR BREAST FEEDING

If pregnant or breast-feeding, ask a health professional before use.

Keep out of reach of children. In case of overdose, get medical help or contact a Poison Control Center right away.

Directions

- take every 4 to 6 hours
- do not exceed 6 doses in 24 hours

adults and children 12 years of age and over | 25 mg to 50 mg (1 to 2 capsules)
children 6 to under 12 years of age | 12.5 mg [12.5 mg dosage strength is not available in this package. Do not attempt to break capsules.] to 25 mg (1 capsule)
children under 6 years of age | ask a doctor

Other information

- store at room temperature 15°-30°C (59°-86°F)
- protect from moisture
- retain carton for complete product information

Inactive ingredients

benzyl alcohol, butylparaben, D&C red #28, edible black ink, FD&C blue #1, FD&C red #40, gelatin, lactose, magnesium stearate, methylparaben, polysorbate 80, propylparaben, sodium lauryl sulfate

PRINCIPAL DISPLAY PANEL

COMPARE TO THE ACTIVE INGREDIENT IN BENADRYL® ALLERGY†

Best Choice®

Antihistamine

Allergy Relief

Actual Size

Diphenhydramine HCl

For Allergy Relief

Sneezing, Itchy, Watery Eyes, Runny Nose, Itchy Throat

24 CAPSULES

25 MG EACH